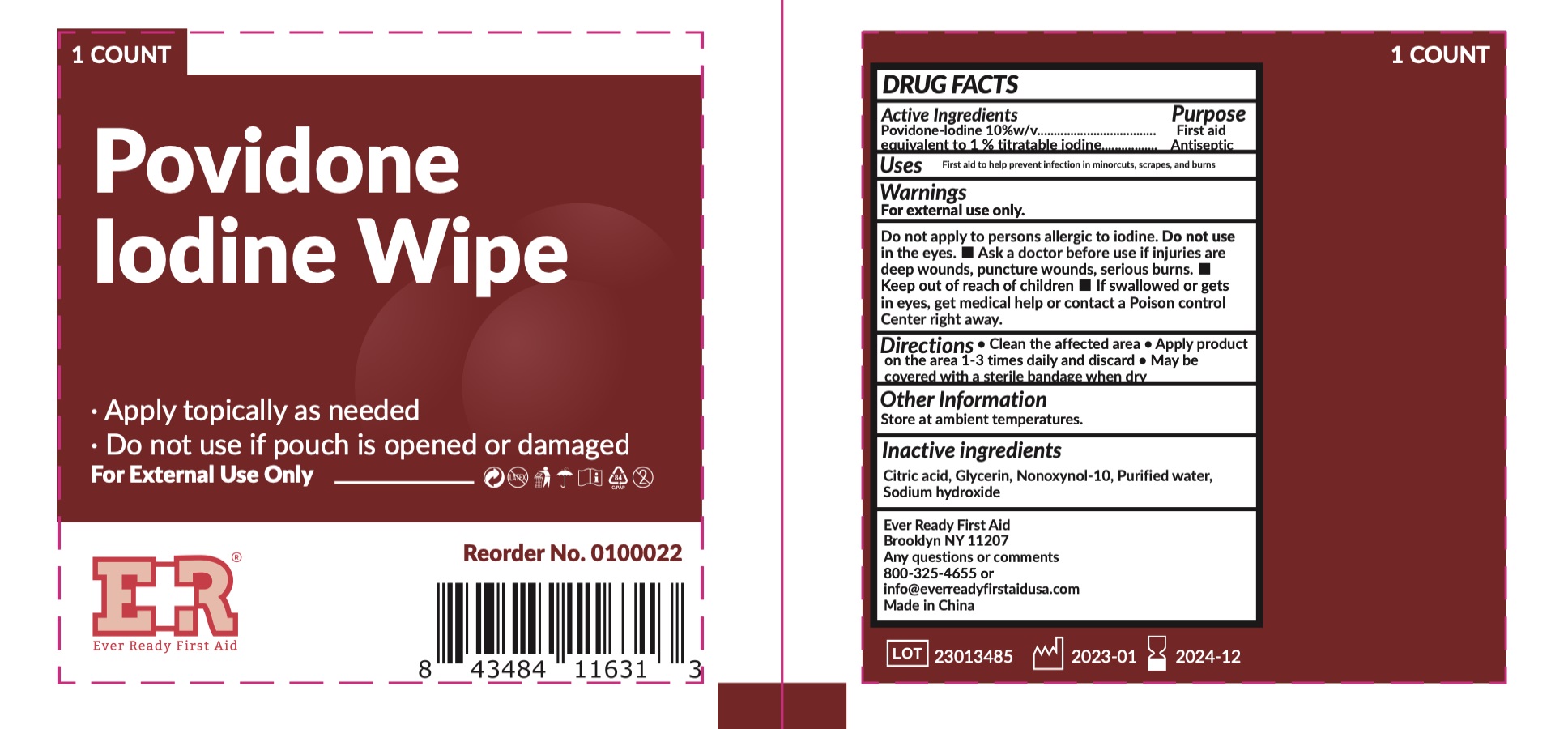 DRUG LABEL: Povidone Iodine Wipe
NDC: 34645-4011 | Form: SWAB
Manufacturer: Jianerkang Medical Co., Ltd
Category: otc | Type: HUMAN OTC DRUG LABEL
Date: 20230202

ACTIVE INGREDIENTS: POVIDONE-IODINE 10 mg/100 mL
INACTIVE INGREDIENTS: CITRIC ACID MONOHYDRATE; GLYCERIN; NONOXYNOL-10; WATER; SODIUM HYDROXIDE

Ever Ready First Aid
Povidone Iodine Wipe

Active Ingredients

Povidone-Iodine 10% w/v (equivalent to 1% titratable iodine)

Purpose

First Aid Antiseptic

Uses

First aid to help prevent infection in minorcuts, scraps, and burns

Warnings

For external use only.

DO NOT USE

Do not apply to persons allergic to iodine. Do not use in the eyes.

Do not use if pouch is opened or damaged

Ask a doctor before use if injuries are deep wounds, puncture wounds, serious burns.

- Keep out of reach of children
- If swallowed or gets in eyes, get medical help or contact a Poison Control Center right away.

Directions

- Clean the affected area
- Apply product on the area 1-3 times daily and discard
- May be covered with a sterile bandage when dry

Inactive ingredients

Citric acid, Glycerin, Nonoxynol-10, Purified water, Sodium hydroxide